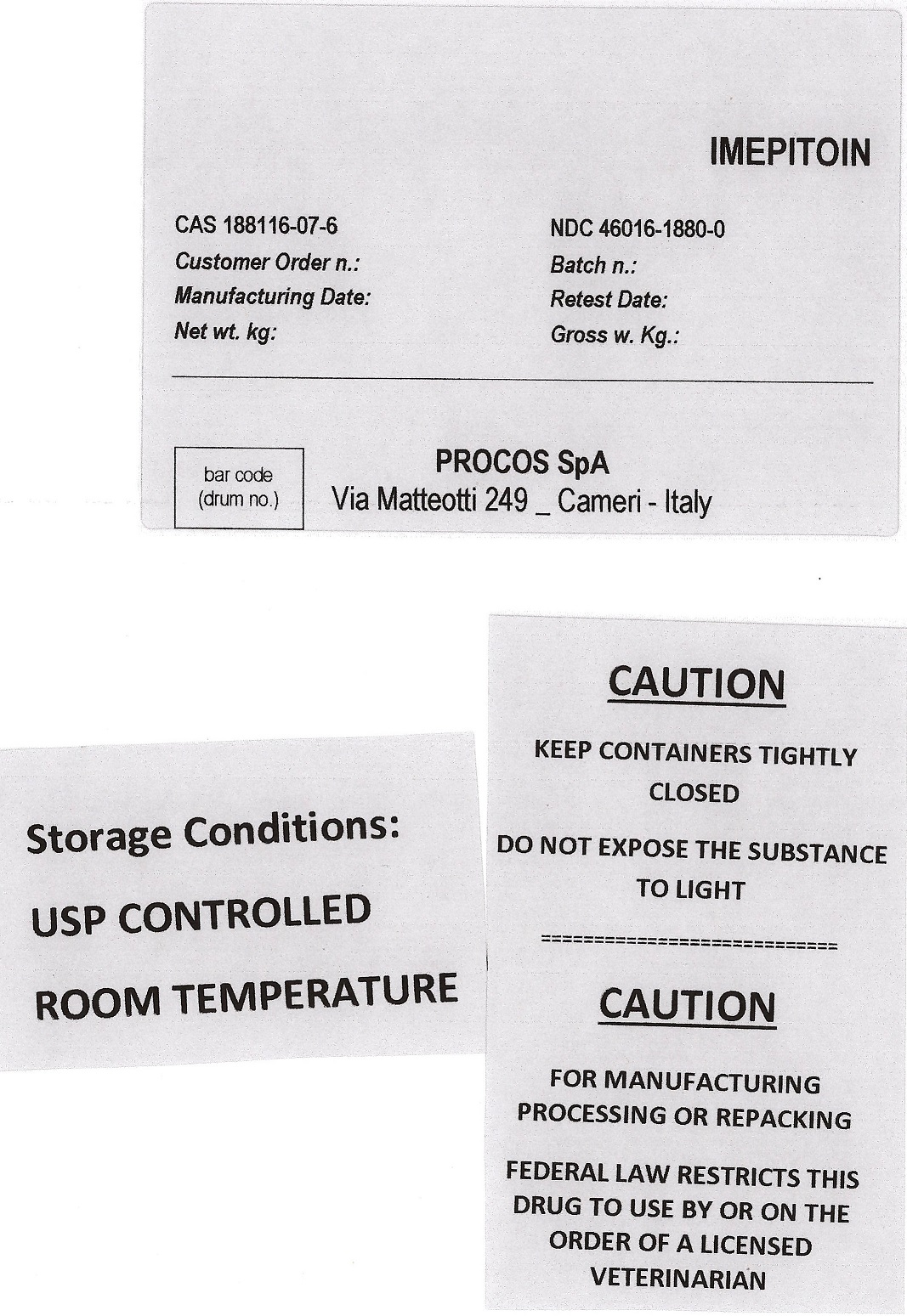 DRUG LABEL: Imepitoin
NDC: 46016-1880 | Form: POWDER
Manufacturer: PROCOS SpA
Category: other | Type: BULK INGREDIENT - ANIMAL DRUG
Date: 20220504

ACTIVE INGREDIENTS: IMEPITOIN 50 kg/50 kg

Imepitoin

PACKAGE LABEL

IMEPITOIN
CAS 188116-07-6 NDC 46016-1880-0

Customer Order n Batch n

Manufacturing Date Retest Date

Net wt. kg. Gross w. Kg.

PROCOS SpA

Via Matteotti 249_Cameri - Italy

CAUTION

KEEP CONTAINERS TIGHTLY CLOSED

DO NOT EXPOSE THE SUBSTANCE TO LIGHT

CAUTION

FOR MANUFACTURING PROCESSING OR REPACKING

FEDERAL LAW RESTRICTS THIS DRUG TO USE BY OR ON THE ORDER OF A LICENSED VETERINARIAN

Storage Conditions:

USP CONTROLLED

ROOM TEMPERATURE